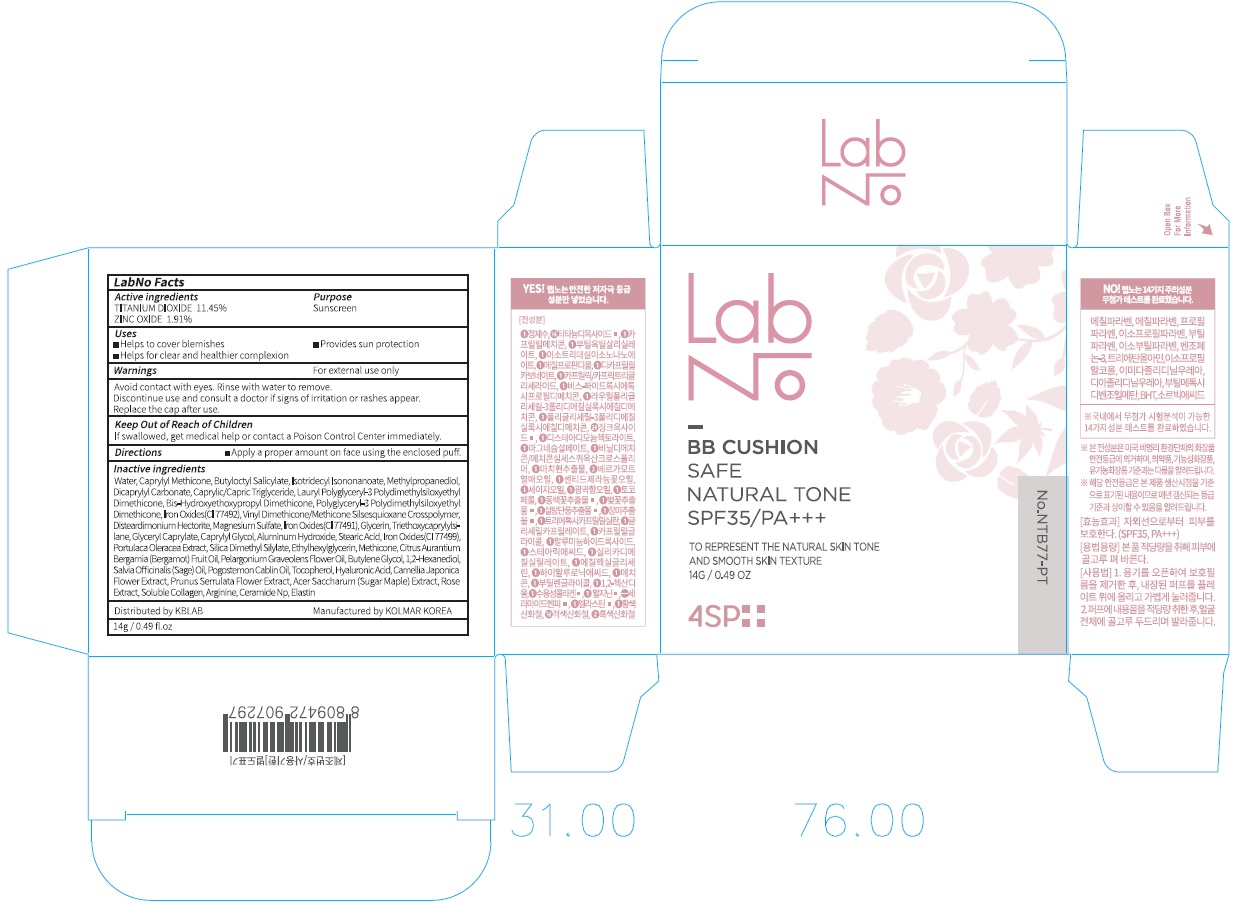 DRUG LABEL: LabNo 4SP Safe Natural Tone BB Cushion
NDC: 71497-020 | Form: POWDER
Manufacturer: KB Lab Co., Ltd.
Category: otc | Type: HUMAN OTC DRUG LABEL
Date: 20170714

ACTIVE INGREDIENTS: Titanium Dioxide 1.60 g/14 g; ZINC OXIDE 0.26 g/14 g
INACTIVE INGREDIENTS: Water; Butyloctyl Salicylate

ACTIVE INGREDIENT

Active ingredients: TITANIUM DIOXIDE 11.45%, ZINC OXIDE 1.91%

INACTIVE INGREDIENT

Inactive ingredients: Water, Caprylyl Methicone, Butyloctyl Salicylate, Isotridecyl Isononanoate, Methylpropanediol, Dicaprylyl Carbonate, Caprylic/Capric Triglyceride, Lauryl Polyglyceryl-3 Polydimethylsiloxyethyl Dimethicone, Bis-Hydroxyethoxypropyl Dimethicone, Polyglyceryl-3 Polydimethylsiloxyethyl Dimethicone, Iron Oxides(CI 77492), Vinyl Dimethicone/Methicone Silsesquioxane Crosspolymer, Disteardimonium Hectorite, Magnesium Sulfate, Iron Oxides(CI 77491), Glycerin, Triethoxycaprylylsilane, Glyceryl Caprylate, Caprylyl Glycol, Aluminum Hydroxide, Stearic Acid, Iron Oxides(CI 77499), Portulaca Oleracea Extract, Silica Dimethyl Silylate, Ethylhexylglycerin, Methicone, Citrus Aurantium Bergamia (Bergamot) Fruit Oil, Pelargonium Graveolens Flower Oil, Butylene Glycol, 1,2-Hexanediol, Salvia Officinalis (Sage) Oil, Pogostemon Cablin Oil, Tocopherol, Hyaluronic Acid, Camellia Japonica Flower Extract, Prunus Serrulata Flower Extract, Acer Saccharum (Sugar Maple) Extract, Rose Extract, Soluble Collagen, Arginine, Ceramide Np, Elastin

PURPOSE

Purpose: Sunscreen

WARNINGS

Warnings: For external use only Avoid contact with eyes. Rinse with water to remove. Discontinue use and consult a doctor if signs of irritation or rashes appear. Replace the cap after use.

Keep Out of Reach of Children If swallowed, get medical help or contact a Poison Control Center immediately.

DESCRIPTION

Uses:

- Helps to cover blemishes

- Helps for clear and healthier complexion

- Provides sun protection

Directions:

Apply a proper amount on face using the enclosed puff.